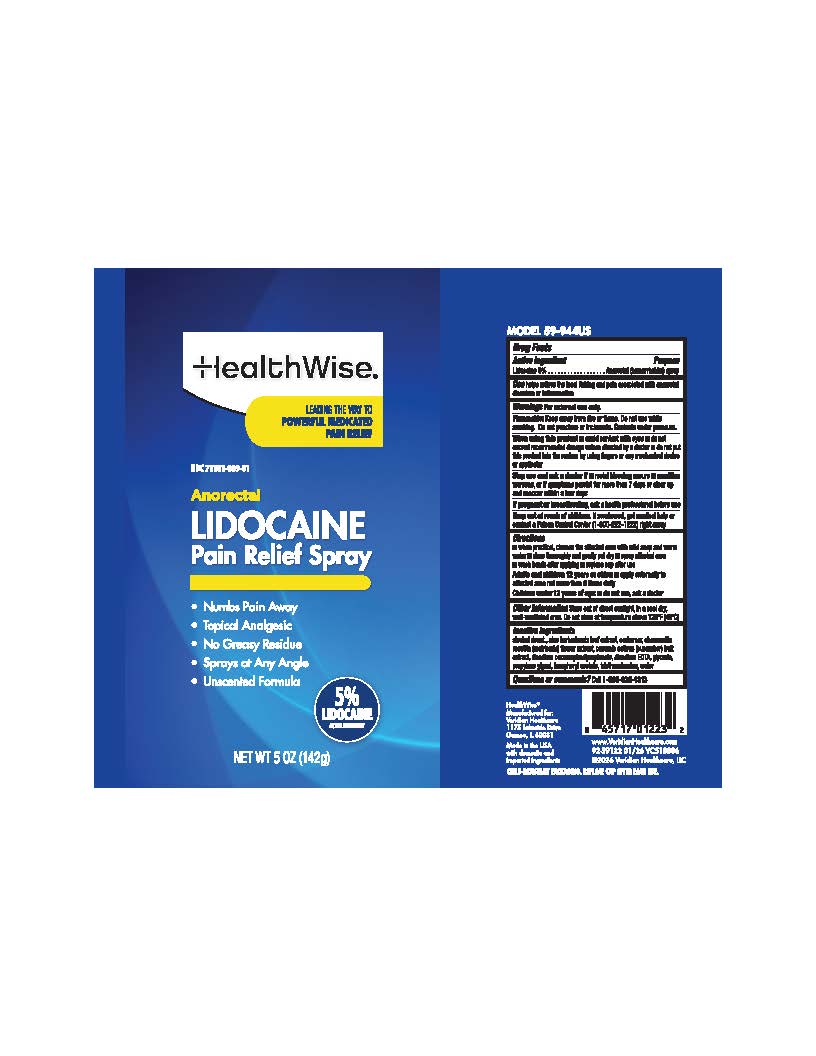 DRUG LABEL: Healthwise Anorectal Pain Relief
NDC: 71101-069 | Form: SPRAY
Manufacturer: Veridian Healthcare
Category: otc | Type: HUMAN OTC DRUG LABEL
Date: 20260106

ACTIVE INGREDIENTS: LIDOCAINE 5 g/100 mL
INACTIVE INGREDIENTS: EDETATE DISODIUM; PROPYLENE GLYCOL; WATER; ALCOHOL; GLYCERIN; ALOE BARBADENSIS LEAF; .ALPHA.-TOCOPHEROL ACETATE; CHAMOMILE; CUCUMBER FRUIT OIL; DISODIUM COCOAMPHODIPROPIONATE; CARBOMER; TRIETHANOLAMINE

Healthwise Anorectal Pain Relief Spray

Drug Facts

Lidocaine 5%

Purpose

Anorectal (hemorrhoidal) spray

Uses

helps relieve the local itching and pain associated with anorectal disorders or inflammation

Warnings

For external use only

FlammableKeep away from fire or flame. Do not use while smokig. Do not punture or incinerate. Contents under presure

Stop use and ask a doctor if

• rectal bleeding occurs

• condition worsens or does not improve within 7 days or clear up and reoccur within a few days

When using this product

• avoid contact with eyes

• do not exceed recommended dosage unless directed by a doctor

• do not put this product into the rectum by using fingers or any mechanical device or applicator

Keep out of reach of children.

If swallowed, get medical help or contact a Poison Control Center (1-800-222-1222) right away.

Directions

• when practical, cleanse the affected area with mild soap and warm water

• rinse thoroughly and gently pat dry

• spray affected area • wash hands after applying

• replace cap after use

• adults and children 12 years and older:apply externally to the affected area not more than 6 times daily

• children under 12 years of age: ask a doctor

Other information

Store out of direct sunlight, in a cool dry, well-ventilated area. Do not store at temperature above 120F (49C)

Inactive ingredients

alcohol denat, aloe barbadensis leaf extract, carbomer, chamomilla recutita (matricaria) flower extract, cucumis sativus (cucumber) fruit extract, disodium cocoamphodipropionate, disodium EDTA, glycerin, propylene glycol, tocopheryl acetate, triethanolamine, water